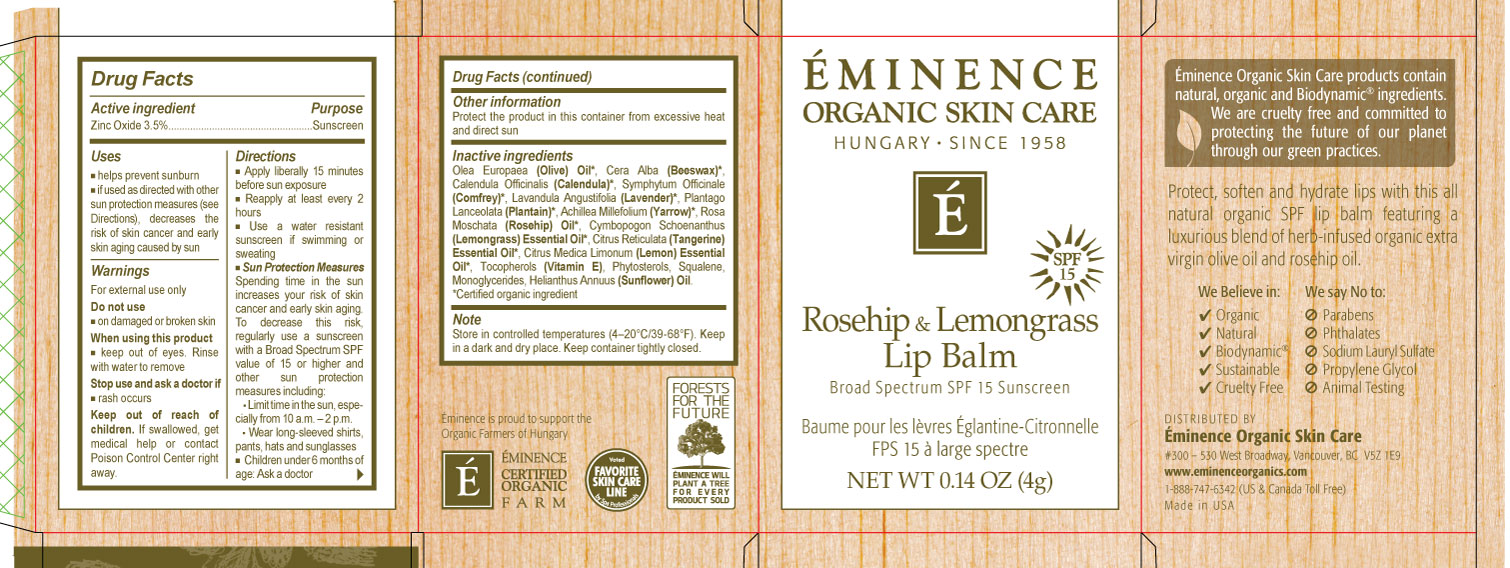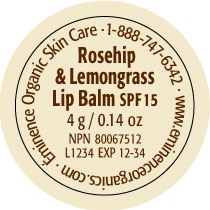 DRUG LABEL: Rosehip and Lemongrass Lip SPF 15
NDC: 15751-1321 | Form: STICK
Manufacturer: Eminence Organic Skin Care
Category: otc | Type: HUMAN OTC DRUG LABEL
Date: 20231130

ACTIVE INGREDIENTS: ZINC OXIDE 35 mg/1 g
INACTIVE INGREDIENTS: OLIVE OIL; YELLOW WAX; COMFREY; PLANTAGO MAJOR; ROSA CANINA FRUIT OIL; WEST INDIAN LEMONGRASS OIL; MANDARIN OIL; LEMON OIL; .ALPHA.-TOCOPHEROL

Rosehip & Lemongrass Lip Balm SPF 15

Active ingredients

Zinc Oxide 3.5%

Purpose

Sunscreen

Uses

- helps prevent sunburn
- if used as directed with other sun protection measures (see), decreases the risk of skin cancer and early skin aging caused by sun Directions

Warnings

For external use only

Do not use

- on damaged or broken skin

When using this product

- keep out of eyes. Rinse with water to remove

Stop use and ask a doctor if

- rash occurs

Keep out of reach of children.

If swallowed, get medical help or contact Poison Control Center right away.

Directions

Apply liberally 15 minutes before sun exposure

- Reapply at least every 2 hou
- Use a water resistant sunscreen if swimming or sweating
- Spending time in the sun increases your risk of skin cancer and early skin aging. To decrease this risk, regularly use a sunscreen with a Broad Spectrum SPF value of 15 or higher and other sun protection measures including: Sun Protection Measures
- Limit time in the sun, especially from 10 a.m. – 2 p.m.
- Wear long-sleeved shirts, pants, hats and sunglasses
- Children under 6 months of age: Ask a doctor

Other information

Protect the product in this container from excessive heat and direct sun

Inactive ingredients

Olive Oil, Beeswax, Calendula, Comfrey, Lavender, Plantain, Yarrow, Rosehip Oil, Lemongrass Oil, Tangerine Oil, Lemon Oil, Vitamin E.